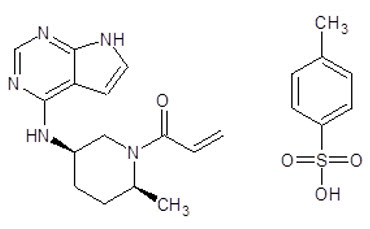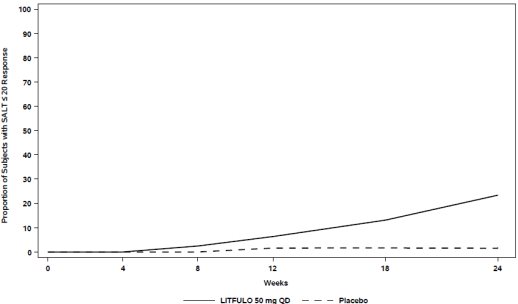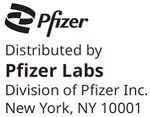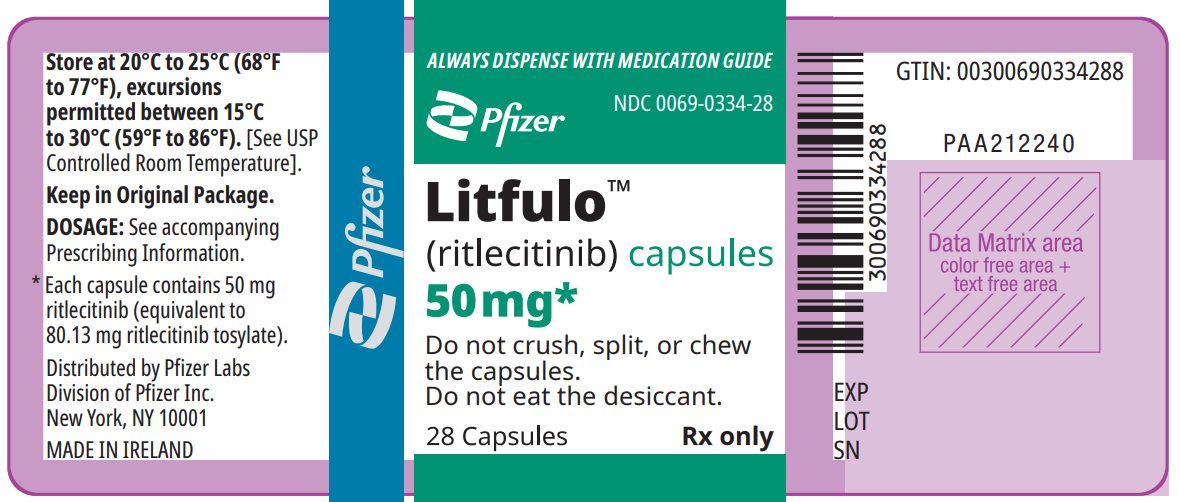 DRUG LABEL: Litfulo
NDC: 0069-0334 | Form: CAPSULE
Manufacturer: Pfizer Laboratories Div Pfizer Inc
Category: prescription | Type: HUMAN PRESCRIPTION DRUG LABEL
Date: 20250522

ACTIVE INGREDIENTS: RITLECITINIB TOSYLATE 50 mg/1 1
INACTIVE INGREDIENTS: CROSPOVIDONE, UNSPECIFIED; GLYCERYL DIBEHENATE; LACTOSE MONOHYDRATE; MICROCRYSTALLINE CELLULOSE; HYPROMELLOSE, UNSPECIFIED; FD&C BLUE NO. 1; TITANIUM DIOXIDE; FERRIC OXIDE YELLOW

HIGHLIGHTS OF PRESCRIBING INFORMATION

These highlights do not include all the information needed to use LITFULO safely and effectively. See full prescribing information for LITFULO.
LITFULO™ (ritlecitinib) capsules, for oral use
Initial U.S. Approval: 2023

WARNING: SERIOUS INFECTIONS, MORTALITY, MALIGNANCY, MAJOR ADVERSE CARDIOVASCULAR EVENTS (MACE), and THROMBOSIS

See full prescribing information for complete boxed warning.

- Increased risk of serious bacterial, fungal, viral, and opportunistic infections that may lead to hospitalization or death, including tuberculosis (TB). Interrupt treatment if serious infection occurs until the infection is controlled. LITFULO should not be given to patients with active tuberculosis. Test for latent TB before and during therapy; start treating latent TB prior to use. Monitor all patients for active TB during treatment, even patients with initial negative, latent TB test. (5.1). Monitor all patients for signs and symptoms of infection during and after treatment with LITFULO. (5.1)
- Higher rate of all-cause mortality, including sudden cardiovascular death with another Janus kinase inhibitor (JAK) vs. TNF blockers in rheumatoid arthritis (RA) patients. LITFULO is not approved for use in RA patients. (5.2)
- Malignancies were reported in patients treated with LITFULO (5.3). Higher rate of lymphomas and lung cancers with another JAK inhibitor vs. TNF blockers in RA patients.
- Higher rate of MACE (defined as cardiovascular death, myocardial infarction, and stroke) with another JAK inhibitor vs. TNF blockers in RA patients. (5.4).
- Thrombosis has occurred in patients treated with LITFULO. Increased incidence of pulmonary embolism, venous and arterial thrombosis with another JAK inhibitor vs. TNF blockers. (5.5)

1 INDICATIONS AND USAGE

LITFULO is a kinase inhibitor indicated for the treatment of severe alopecia areata in adults and adolescents 12 years and older. (1)

Limitations of Use: Not recommended for use in combination with other JAK inhibitors, biologic immunomodulators, cyclosporine or other potent immunosuppressants (1).

2 DOSAGE AND ADMINISTRATION

- For recommended testing, evaluations and immunizations prior to LITFULO initiation, see Full Prescribing Information. (2.1)
- Recommended dosage is 50 mg orally once daily. (2.2)
- For dosage interruption for certain adverse reactions, see Full Prescribing Information. (2.4)

3 DOSAGE FORMS AND STRENGTHS

Capsules: 50 mg of ritlecitinib (3)

4 CONTRAINDICATIONS

LITFULO is contraindicated in patients with known hypersensitivity to ritlecitinib or any of its excipients. (4)

5 WARNINGS AND PRECAUTIONS

- Hypersensitivity: Discontinue LITFULO if a clinically significant hypersensitivity reaction occurs. (5.6)
- Laboratory Abnormalities: Perform ALC and platelet counts prior to LITFULO initiation. Treatment interruption or discontinuation are recommended based on ALC and platelet count abnormalities. (5.7)
- Vaccinations: Avoid use of live vaccines during or shortly prior to LITFULO treatment. (5.8)

6 ADVERSE REACTIONS

Most common adverse reactions (incidence ≥1%) are headache, diarrhea, acne, rash, urticaria, folliculitis, pyrexia, atopic dermatitis, dizziness, blood creatine phosphokinase increased, herpes zoster, red blood cell count decreased, and stomatitis. (6.1)

To report SUSPECTED ADVERSE REACTIONS, contact Pfizer Inc. at 1-800-438-1985 or FDA at 1-800-FDA-1088 or www.fda.gov/medwatch.

7 DRUG INTERACTIONS

- Certain CYP3A substrates: Additional monitoring and dose adjustment of CYP3A substrate should be considered. (7.1)
- Certain CYP1A2 substrates: Additional monitoring and dose adjustment of CYP1A2 substrate should be considered. (7.1)
- Certain CYP3A inducers: Coadministration with strong inducers of CYP3A is not recommended. (7.2)

8 USE IN SPECIFIC POPULATIONS

- Lactation: Breastfeeding not recommended. (8.2)
- Severe Hepatic Impairment: Not recommended. (8.6)

FULL PRESCRIBING INFORMATION

WARNING: SERIOUS INFECTIONS, MORTALITY, MALIGNANCY, MAJOR ADVERSE CARDIOVASCULAR EVENTS (MACE), and THROMBOSIS

- Increased risk of serious bacterial, fungal, viral and opportunistic infections leading to hospitalization or death, including tuberculosis (TB). Interrupt treatment if serious infection occurs until the infection is controlled. LITFULO should not be given to patients with active tuberculosis. Test for latent TB before and during therapy; treat latent TB prior to use. Monitor all patients for active TB during treatment, even patients with initial negative, latent TB test. (5.1)
- Higher rate of all-cause mortality, including sudden cardiovascular death with another Janus kinase inhibitor (JAK) vs. TNF blockers in rheumatoid arthritis (RA) patients. LITFULO is not approved for use in RA patients. (5.2)
- Malignancies have occurred in patients treated with LITFULO [see Warnings and Precautions (5.3)]. Higher rate of lymphomas and lung cancers with another JAK inhibitor vs. TNF blockers in RA patients. (5.3)
- Higher rate of MACE (defined as cardiovascular death, myocardial infarction, and stroke) with another JAK inhibitor vs. TNF blockers in RA patients. (5.4)
- Thrombosis has occurred in patients treated with LITFULO. Increased incidence of pulmonary embolism, venous and arterial thrombosis with another JAK inhibitor vs. TNF blockers. (5.5)

1 INDICATIONS AND USAGE

LITFULO is a kinase inhibitor indicated for the treatment of severe alopecia areata in adults and adolescents 12 years and older.

Limitations of Use: Not recommended for use in combination with other JAK inhibitors, biologic immunomodulators, cyclosporine or other potent immunosuppressants.

2 DOSAGE AND ADMINISTRATION

2.1 Recommended Evaluations and Immunizations Prior to Treatment Initiation

Perform the following evaluations prior to LITFULO initiation:

- Tuberculosis (TB) infection evaluation: LITFULO initiation is not recommended in patients with active TB. For patients with latent TB or those with a negative latent TB test who are at high risk for TB, start preventive therapy for latent TB prior to initiation of LITFULO [see Warnings and Precautions (5.1)].
- Viral hepatitis screening in accordance with clinical guidelines: LITFULO initiation is not recommended in patients with hepatitis B or hepatitis C [see Warnings and Precautions (5.1)].
- Treatment with LITFULO should not be initiated in patients with an absolute lymphocyte count (ALC) <500/mm^3 or a platelet count <100,000/mm^3 [see Warnings and Precautions (5.7)].
- Update immunizations according to current immunization guidelines [see Warnings and Precautions (5.8)].

2.2 Recommended Dosage

The recommended dosage of LITFULO is 50 mg orally once daily with or without food [see Clinical Pharmacology (12.3)].

Swallow capsules whole. Do not crush, split, or chew LITFULO capsules.

If a dose is missed, administer the dose as soon as possible unless it is less than 8 hours before the next dose, in which case, skip the missed dose. Thereafter, resume dosing at the regular scheduled time.

2.3 Patients with Severe Hepatic Impairment

LITFULO is not recommended in patients with severe (Child Pugh C) hepatic impairment [see Use in Specific Populations (8.6) and Clinical Pharmacology (12.3)].

2.4 Treatment Interruption or Discontinuation

If treatment interruption is indicated, a temporary treatment interruption for less than 6 weeks is not expected to result in significant loss of regrown scalp hair.

Hematologic Abnormalities

Recommendations for LITFULO treatment interruption or discontinuation for hematologic abnormalities are summarized in Table 1.

Table 1. Laboratory Monitoring Guidance
Laboratory Measure | Recommendation
Platelet Count | Treatment should be discontinued if platelet count is <50,000/mm^3
Lymphocytes | Treatment should be interrupted if ALC is <500/mm^3 and may be restarted once ALC return above this value.
ALC = absolute lymphocyte count.

ALC and platelet counts are recommended before treatment initiation and at 4 weeks after treatment initiation, and thereafter according to routine patient management [see Warnings and Precautions (5.7)].

3 DOSAGE FORMS AND STRENGTHS

Capsules: 50 mg of ritlecitinib, size 3, opaque capsules with yellow body and blue cap. The body is printed with “RCB 50” and the cap is printed with “Pfizer” in black.

4 CONTRAINDICATIONS

LITFULO is contraindicated in patients with known hypersensitivity to ritlecitinib or any of its excipients [see Warnings and Precautions (5.6)].

5 WARNINGS AND PRECAUTIONS

5.1 Serious Infections

Serious infections have been reported in patients receiving LITFULO. The most frequent serious infections have been appendicitis, COVID-19 infection (including pneumonia), and sepsis [see Adverse Reactions (6.1)]. Among opportunistic infections, multi-dermatomal herpes zoster was reported with LITFULO.

Avoid use of LITFULO in patients with an active, serious infection. Consider the risks and benefits of treatment prior to initiating LITFULO in patients:

- with chronic or recurrent infection
- who have been exposed to TB
- with a history of serious infection or an opportunistic infection
- who have resided or traveled in areas of endemic TB or mycoses, or
- with underlying conditions that may predispose them to infection

Closely monitor patients for the development of signs and symptoms of infection during and after treatment with LITFULO. Interrupt LITFULO if a patient develops a serious or opportunistic infection. A patient who develops a new infection during treatment with LITFULO should undergo prompt and complete diagnostic testing appropriate for an immunocompromised patient, appropriate antimicrobial therapy should be initiated, and the patient should be closely monitored. LITFULO may be resumed once the infection is controlled.

Tuberculosis

Screen patients for tuberculosis (TB) before starting therapy. LITFULO should not be given to patients with active TB. Anti-TB therapy should be started prior to initiating therapy with LITFULO in patients with a new diagnosis of latent TB or previously untreated latent TB. In patients with a negative latent TB test, consider anti-TB therapy before initiating treatment with LITFULO in those at high risk and consider screening patients at high risk for TB during treatment with LITFULO.

Viral Reactivation

Viral reactivation, including cases of herpes virus reactivation (e.g., herpes zoster), was reported in clinical trials [see Adverse Reactions (6.1)]. If a patient develops herpes zoster, consider interrupting treatment until the episode resolves.

Screening for viral hepatitis should be performed in accordance with clinical guidelines before starting therapy with LITFULO. Patients with evidence of HIV infection or hepatitis B or C infection were excluded from clinical trials.

5.2 Mortality

In a large, randomized, postmarketing safety study of another JAK inhibitor in RA patients 50 years of age and older with at least one cardiovascular risk factor, a higher rate of all-cause mortality, including sudden cardiovascular death, was observed in patients treated with the JAK inhibitor compared with TNF blockers. Consider the benefits and risks for the individual patient prior to initiating or continuing therapy with LITFULO.

5.3 Malignancy and Lymphoproliferative Disorders

Malignancies, including non-melanoma skin cancer (NMSC), were observed in clinical trials of LITFULO [see Adverse Reactions (6.1)].

In a large, randomized, postmarketing safety study of another JAK inhibitor in RA patients, a higher rate of malignancies (excluding non-melanoma skin cancer (NMSC)) was observed in patients treated with the JAK inhibitor compared to those treated with TNF blockers. A higher rate of lymphomas was observed in patients treated with the JAK inhibitor compared to those treated with TNF blockers. A higher rate of lung cancers was observed in current or past smokers treated with the JAK inhibitor compared to those treated with TNF blockers. In this study, current or past smokers had an additional increased risk of overall malignancies.

The risks and benefits of ritlecitinib treatment should be considered prior to initiating or continuing therapy in patients with a known malignancy other than a successfully treated NMSC or cervical cancer.

Periodic skin examination is recommended for patients who are at increased risk for skin cancer.

5.4 Major Adverse Cardiovascular Events (MACE)

In a large, randomized, postmarketing safety study of another JAK inhibitor in RA patients 50 years of age and older with at least one cardiovascular risk factor, a higher rate of major adverse cardiovascular events (MACE) defined as cardiovascular death, non-fatal myocardial infarction (MI), and non-fatal stroke was observed with the JAK inhibitor compared to those treated with TNF blockers. Patients who are current or past smokers are at additional increased risk.

Consider the benefits and risks for the individual patient prior to initiating or continuing therapy with LITFULO, particularly in patients who are current or past smokers and patients with other cardiovascular risk factors. Patients should be informed about the symptoms of serious cardiovascular events and the steps to take if they occur. Discontinue LITFULO in patients that have experienced a myocardial infarction or stroke.

5.5 Thromboembolic Events

An event of pulmonary embolism (PE) was reported in a patient receiving LITFULO [see Adverse Reactions (6.1)]. In a ritlecitinib higher dosing group, 1 patient reported an event of retinal artery occlusion.

In a large, randomized, postmarketing safety study of another JAK inhibitor in RA patients 50 years of age and older with at least one cardiovascular risk factor, higher rates of overall thrombosis, DVT, and PE were observed compared to those treated with TNF blockers.

Avoid LITFULO in patients who may be at increased risk of thrombosis. If symptoms of thrombosis or embolism occur, patients should interrupt LITFULO and be evaluated promptly and treated appropriately.

5.6 Hypersensitivity

Serious reactions including anaphylactic reactions, urticaria and rash have been observed in patients receiving LITFULO in clinical trials. If a clinically significant hypersensitivity reaction occurs, discontinue LITFULO and institute appropriate therapy [see Adverse Reactions (6.1)].

5.7 Laboratory Abnormalities

Treatment with LITFULO was associated with decreases in lymphocytes and platelets [see Adverse Reactions (6.1)].

Prior to LITFULO initiation, perform ALC and platelet counts [see Dosage and Administration (2.1)]. After initiating treatment with LITFULO, treatment interruption or discontinuation are recommended based on ALC and platelet count abnormalities [see Dosage and Administration (2.4)].

Liver Enzyme Elevations – Treatment with LITFULO was associated with increased incidence of liver enzyme elevation compared to placebo. Increases of ALT ≥5 times the upper limit of normal (ULN) and increases of AST ≥5 times the ULN were observed in patients in LITFULO clinical trials. Evaluate at baseline and thereafter according to routine patient management. Prompt investigation of the cause of liver enzyme elevation is recommended to identify potential cases of drug-induced liver injury. If increases in ALT or AST are observed and drug-induced liver injury is suspected, interrupt LITFULO until this diagnosis is excluded.

Creatine Phosphokinase (CPK) Elevations – Treatment with LITFULO was associated with increased incidence of CPK elevation compared to placebo.

5.8 Vaccinations

No data are available on the response to vaccination in patients receiving LITFULO. Use of live attenuated vaccines should be avoided during or shortly prior to initiating treatment. Prior to initiating LITFULO, it is recommended that patients be brought up to date with all immunizations, including prophylactic herpes zoster vaccinations, in agreement with current immunization guidelines.

6 ADVERSE REACTIONS

The following clinically significant adverse reactions are described elsewhere in the labeling:

- Serious Infections [see Warnings and Precautions (5.1)]
- Malignancy and Lymphoproliferative Disorders [see Warnings and Precautions (5.3)]
- Thromboembolic Events [see Warnings and Precautions (5.5)]
- Hypersensitivity [see Warnings and Precautions (5.6)]
- Laboratory Abnormalities [see Warnings and Precautions (5.7)]

6.1 Clinical Trials Experience

Because clinical trials are conducted under widely varying conditions, adverse reaction rates observed in the clinical trials of a drug cannot be directly compared to rates in the clinical trials of another drug and may not reflect the rates observed in practice.

The safety of LITFULO was evaluated in three randomized, placebo-controlled clinical trials and one long-term trial in subjects with alopecia areata, including alopecia totalis and alopecia universalis, who were 12 years of age and older. A total of 1628 subjects were treated with LITFULO representing 2085 subject-years of exposure. There were 1011 subjects with at least 1 year of exposure to LITFULO. In the placebo-controlled period of clinical trials in alopecia areata, a total of 668 subjects were exposed to LITFULO with 130 receiving 50 mg once daily for up to 24 weeks. The median age of subjects was 33 years, 105 (11.9%) subjects were 12 to <18 years old and 22 (2.5%) subjects were 65 years of age or older. The majority of subjects were White (70.7%) and female (63.6%).

Adverse reactions occurring at ≥1% in the treated groups and at a higher rate than placebo are presented in Table 2. A total of 2 (1.5%) subjects treated with LITFULO 50 mg were discontinued from the trials due to adverse reactions.

Table 2. Adverse Reactions in Clinical Trials of LITFULO for the Treatment of Alopecia Areata [Reported in ≥1% of subjects and at a higher rate than placebo for up to 24 weeks.]
 | LITFULO 50 mg N=130 n (%) | Placebo N=213 n (%)
Headache [Headache includes headache and migraine.] | 14 (10.8) | 18 (8.5)
Diarrhea [Diarrhea includes diarrhea and frequent bowel movements.] | 13 (10.0) | 8 (3.8)
Acne [Acne includes acne and acne pustular.] | 8 (6.2) | 10 (4.7)
Rash [Rash includes rash and dermatitis allergic.] | 7 (5.4) | 2 (0.9)
Urticaria | 6 (4.6) | 3 (1.4)
Folliculitis | 4 (3.1) | 4 (1.9)
Pyrexia | 4 (3.1) | 0
Dermatitis atopic | 3 (2.3) | 1 (0.5)
Dizziness | 3 (2.3) | 3 (1.4)
Blood creatine phosphokinase increased | 2 (1.5) | 0
Herpes zoster | 2 (1.5) | 0
Red blood cell count decreased | 2 (1.5) | 0
Stomatitis | 2 (1.5) | 0

Specific Adverse Reactions

Exposure adjusted incidence rates were adjusted by clinical trial size for all adverse reactions reported in this section.

Overall Infections

In the placebo-controlled trials, for up to 24 weeks, overall infections were reported in 66 subjects (80.35 per 100 subject-years) treated with placebo and 43 subjects (74.53 per 100 subject-years) treated with LITFULO 50 mg. Across clinical trials, including the long-term trial, overall infections were reported in 645 subjects (50.71 per 100 subject-years) treated with LITFULO 50 mg or higher.

Serious Infections

In the placebo-controlled trials, for up to 24 weeks, 3 subjects reported serious infections across all ritlecitinib doses studied. Across clinical trials, including the long-term trial, serious infections were reported in 12 subjects (0.66 per 100 subject-years) treated with LITFULO 50 mg or higher. The most common serious infections were related to appendicitis, COVID-19 infection (including pneumonia), and sepsis.

Herpes Zoster

In the placebo-controlled trials, for up to 24 weeks, herpes zoster was reported in 4 subjects across all ritlecitinib doses studied and 0 subjects treated with placebo. Across clinical trials, including the long-term trial, herpes zoster was reported in 21 subjects (1.17 per 100 subject-years) treated with LITFULO 50 mg or higher. Opportunistic infections of multi-dermatomal herpes zoster were reported in 1 subject (0.50 per 100 subject-years) treated with the ritlecitinib higher dose in the placebo-controlled trials and 2 subjects (0.1 per 100 subject-years) treated with LITFULO 50 mg or higher in all clinical trials.

Malignancy

In the placebo-controlled trials, for up to 24 weeks, 1 malignancy (breast cancer) was reported in 1 subject (1.33 per 100 subject-years) treated with ritlecitinib higher dose and no malignancy was reported in subjects treated with placebo. Across clinical trials, including the long-term trial, malignancies excluding NMSC were reported in 7 subjects (0.37 per 100 subject-years) treated with LITFULO 50 mg or higher.

Thromboembolic Events

Across clinical trials, including the long-term trial, pulmonary embolism (PE) was reported in 1 subject (0.06 per 100 subject-years) treated with LITFULO. There was 1 report of retinal artery occlusion and 1 report of acute myocardial infarction.

Urticaria

In the placebo-controlled trials, for up to 24 weeks, urticaria was reported in 28 subjects treated in all ritlecitinib doses studied and 3 subjects treated with placebo. The rate of urticaria was 8.23 per 100 subject-years in subjects treated with ritlecitinib 50 mg and 4.03 per 100 subject-years in subjects treated with placebo. Across clinical trials, including the long-term trial, urticaria was reported in 76 subjects treated with LITFULO 50 mg or higher. Among all subjects treated with ritlecitinib 50 mg or higher in the integrated safety analysis, the rate of urticaria was 4.10 per 100 subject-years. The median time to onset of an initial event was 8 weeks; median duration of urticaria was 7 days. Most of the cases were mild to moderate in severity.

Decreased Lymphocyte Counts

Across clinical trials, including the long-term trial confirmed ALC <500/mm^3 occurred in 1 subject (<0.1%) treated with LITFULO 50 mg. Age appeared to be a risk factor for lower ALC in subjects ≥65 years of age.

Decreased Platelet Count

In the placebo-controlled trials, for up to 24 weeks, treatment with LITFULO was associated with a decrease in platelet count. Maximum effects on platelets were observed within 4 weeks, after which platelet count remained stable at a lower level with continued therapy. Across clinical trials, including the long-term trial, 1 subject (<0.1%) had a confirmed platelet count <100,000/mm^3. No subject had a confirmed platelet count <75,000/mm^3.

Creatine Phosphokinase (CPK) Elevations

In the placebo-controlled trials, for up to 24 weeks, events of blood CPK increased were reported in 2 (1.5%) subjects treated with LITFULO 50 mg and 0 subjects treated with placebo.

Liver Enzyme Elevations

In the placebo-controlled trials, for up to 24 weeks, events of increases in liver enzymes ≥3 times the upper limit of normal (ULN) were observed in subjects treated with LITFULO [see Warnings and Precautions (5.7)].

7 DRUG INTERACTIONS

7.1 Effects of LITFULO on Other Drugs

Table 3 includes clinically significant drug interactions affecting other drugs.

Table 3. Clinically Significant Interactions Affecting Other Drugs
CYP3A Substrates Where Small Concentration Changes May Lead to Serious Adverse Reactions
Clinical Impact | Ritlecitinib is a CYP3A inhibitor. Concomitant use of ritlecitinib increases AUC and Cmax of CYP3A substrates [see Clinical Pharmacology (12.3)], which may increase the risk of adverse reactions of these substrates.
Intervention | Consider additional monitoring and dosage adjustment in accordance with approved product labeling of CYP3A substrates where small concentration changes may lead to serious adverse reactions when used with LITFULO.
CYP1A2 Substrates Where Small Concentration Changes May Lead to Serious Adverse Reactions
Clinical Impact | Ritlecitinib is a CYP1A2 inhibitor. Concomitant use of ritlecitinib increases AUC and Cmax of CYP1A2 substrates [see Clinical Pharmacology (12.3)], which may increase the risk of adverse reactions of these substrates.
Intervention | Consider additional monitoring and dosage adjustment in accordance with the approved product labeling of CYP1A2 substrates where small concentration changes may lead to serious adverse reactions when used concomitantly with LITFULO.

7.2 Effects of Other Drugs on LITFULO

Table 4 includes clinically significant drug interactions affecting LITFULO.

Table 4. Clinically Significant Interactions Affecting LITFULO
CYP3A Inducers
Clinical Impact | Concomitant use of strong CYP3A inducer (e.g., rifampin) may decrease AUC and Cmax of ritlecitinib [see Clinical Pharmacology (12.3)], which may result in loss of or reduced clinical response.
Intervention | Coadministration with strong inducers of CYP3A is not recommended.

8 USE IN SPECIFIC POPULATIONS

8.1 Pregnancy

Pregnancy Exposure Registry

If a patient becomes pregnant while receiving LITFULO, healthcare providers should report LITFULO exposure by calling 1-877-390-2940.

Risk Summary

Available data from clinical trials with LITFULO use in pregnant women are insufficient to identify a drug-associated risk of major birth defects, miscarriage or other adverse maternal or fetal outcomes. In animal reproduction studies, oral administration of ritlecitinib to pregnant rats and rabbits during organogenesis caused fetotoxicity and fetal malformations at exposures 49 and 55 times the maximum recommended human dose (MRHD) based on area under the curve (AUC) comparison, respectively (see Animal Data).

The background risks of major birth defects and miscarriage for the indicated population are unknown. All pregnancies carry some risk of birth defects, loss, or other adverse outcomes. The estimated background risks in the U.S. general population of major birth defects and miscarriages are 2-4% and 15-20% of clinically recognized pregnancies, respectively.

Data

Animal Data

In an embryo-fetal development study in pregnant rats, oral administration of ritlecitinib from gestation days 6 to 17 decreased fetal body weights and caused fetal skeletal malformations (malformed vertebrae and ribs) and variations (delayed ossification) at doses ≥175 mg/kg/day (49 times the MRHD based on AUC comparison). Maternal toxicity (lower body weights) was noted at 325 mg/kg/day (102 times the MRHD based on AUC comparison). There was no developmental toxicity at 75 mg/kg/day (16 times the MRHD based on AUC comparison).

In an embryo-fetal development study in pregnant rabbits, oral administration of ritlecitinib from gestation days 7 to 19 decreased mean fetal body weights and increased visceral malformations (malpositioned kidneys), skeletal malformations (supernumerary sternebrae, absent thoracic arch, and/or fused thoracic centra), and skeletal variations (delayed ossification) at 75 mg/kg/day (55 times the MRHD based on AUC comparison). There was no developmental toxicity at doses up to 25 mg/kg/day (12 times the MRHD based on AUC comparison).

In a pre- and postnatal development study in rats, oral administration of ritlecitinib from gestation day 6 through lactation day 20 had no effects on pre- and postnatal development at doses up to 75 mg/kg/day (14 times the MRHD based on AUC comparison). At 175 mg/kg/day (41 times the MRHD based on AUC comparison), ritlecitinib caused adverse lower postnatal survival and lower offspring body weights, which correlated with delayed sexual maturation in both sexes. Bred females in the F1 generation also exhibited lower mean numbers of corpora lutea at 175 mg/kg/day.

8.2 Lactation

Risk Summary

There are no data on the presence of ritlecitinib in human milk, the effects on the breastfed infant, or the effects on milk production. Ritlecitinib is present in the milk of lactating rats (see Data). When a drug is present in animal milk, it is likely that it will be present in human milk. Because of the serious adverse effects in adults, including risks of serious infection and malignancy, advise women not to breastfeed during treatment with LITFULO and for approximately 14 hours after the last dose (approximately 6 elimination half-lives).

Data

After a single oral 30 mg/kg dose of ritlecitinib to lactating rats, ritlecitinib concentrations in milk over time were higher than those in plasma. The mean milk to plasma AUC ratio was 2.2.

8.4 Pediatric Use

The safety and effectiveness of LITFULO for the treatment of alopecia areata have been established in pediatric patients ages 12 years and older. A total of 181 pediatric patients ages 12 to <18 years were enrolled in alopecia areata clinical trials, with 105 pediatric patients ages 12 to <18 years with alopecia areata randomized in a pivotal, double-blind, placebo-controlled trial (Trial AA-I). Efficacy was consistent between the pediatric patients and adults [see Clinical Studies (14)]. The adverse reaction profile in the pediatric patients was similar to adults.

The safety and efficacy of LITFULO have not been established in pediatric patients under 12 years of age.

8.5 Geriatric Use

No dose adjustment is required for patients ≥65 years of age.

A total of 28 patients enrolled in alopecia areata trials were 65 years of age and older, and none were 75 years of age and older. Clinical trials of LITFULO did not include sufficient numbers of patients 65 years of age and older to determine whether they respond differently from younger adult patients.

As there is a higher incidence of infections in the elderly population in general, caution should be used when treating the elderly.

8.6 Hepatic Impairment

No dose adjustment is required in patients with mild (Child Pugh A) or moderate (Child Pugh B) hepatic impairment.

LITFULO is not recommended in patients with severe (Child Pugh C) hepatic impairment [see Dosage and Administration (2.3) and Clinical Pharmacology (12.3)].

10 OVERDOSAGE

LITFULO was administered in clinical trials up to a single oral dose of 800 mg. Adverse reactions were comparable to those seen at lower doses and no specific toxicities were identified. Pharmacokinetics (PK) data up to and including a single oral dose of 800 mg in healthy adult volunteers indicate that more than 90% of the administered dose is expected to be eliminated within 48 hours.

There is no specific antidote for overdose with LITFULO. Treatment should be symptomatic and supportive, and monitor patients for signs and symptoms of adverse reactions [see Clinical Trials Experience (6.1)].

In case of an overdose, call Poison Control Center at 1-800-222-1222 for latest recommendations.

11 DESCRIPTION

LITFULO (ritlecitinib) capsules are formulated with ritlecitinib tosylate, a kinase inhibitor.

Ritlecitinib tosylate is a white to off white to pale pink solid which is freely soluble in water. The chemical name is 1-{(2S,5R)-2-Methyl-5-[(7H-pyrrolo[2,3-d]pyrimidin-4-yl)amino]piperidin-1-yl}prop-2-en-1-one 4 methylbenzene-1-sulfonic acid.

The molecular formula for ritlecitinib tosylate is C22H27N5O4S. The molecular weight is 457.55 g/mol and its structural formula is:

LITFULO is supplied for oral administration as a 50 mg immediate-release capsule. Each capsule contains 50 mg ritlecitinib (equivalent to 80.13 mg ritlecitinib tosylate) and the following inactive ingredients: crospovidone, glyceryl dibehenate, lactose monohydrate, microcrystalline cellulose, and hypromellose (HPMC) capsule shells. The yellow/blue, opaque capsule shells contain Brilliant blue FCF – FD&C Blue, hypromellose, titanium dioxide, and yellow iron oxide.

12 CLINICAL PHARMACOLOGY

12.1 Mechanism of Action

LITFULO is a kinase inhibitor.

Ritlecitinib irreversibly inhibits Janus kinase 3 (JAK3) and the tyrosine kinase expressed in hepatocellular carcinoma (TEC) kinase family by blocking the adenosine triphosphate (ATP) binding site. In cellular settings, ritlecitinib inhibits cytokine induced STAT phosphorylation mediated by JAK3-dependent receptors. Additionally, ritlecitinib inhibits signaling of immune receptors dependent on TEC kinase family members. The relevance of inhibition of specific JAK or TEC family enzymes to therapeutic effectiveness is not currently known.

12.2 Pharmacodynamics

Lymphocyte Subsets

A dose-dependent early decrease in absolute lymphocyte levels, T lymphocytes (CD3) and T lymphocyte subsets (CD4 and CD8) was associated with LITFULO treatment in patients with alopecia areata. In addition, there was a dose-dependent early decrease in NK cells (CD16/56) which remained stable at the lower level up to Week 48. For the 50 mg QD dose, there was an initial decrease in median lymphocyte levels which remained consistent up to Week 48. There was no change observed in B lymphocytes (CD19) in any treatment group.

Cardiac Electrophysiology

At 12 times the mean maximum exposure of the 50 mg once daily dose in patients with alopecia areata, there was no clinically relevant effect on the QTc interval.

12.3 Pharmacokinetics

Ritlecitinib AUC0-tau and Cmax increase in an approximately dose-proportional manner up to 200 mg. Steady state was reached approximately by Day 4.

Absorption

The ritlecitinib absolute oral bioavailability is approximately 64%. Ritlecitinib peak plasma concentrations were reached within 1 hour following an oral dose.

Effect of Food

Food does not have a clinically significant impact on the systemic exposures of ritlecitinib. The coadministration of a 100 mg ritlecitinib capsule with a high-fat meal reduced the ritlecitinib Cmax by ~32% and AUCinf was increased by 11%. In clinical trials, ritlecitinib was administered without regard to meals [see Dosage and Administration (2.2)].

Distribution

Approximately 14% of circulating ritlecitinib is bound to plasma proteins.

Elimination

The ritlecitinib mean terminal half-life ranges from 1.3 to 2.3 hours.

Metabolism

The metabolism of ritlecitinib is mediated by multiple pathways with no single route contributing to more than 25% of the total metabolism. These pathways include:

- Glutathione S-transferase (GST): cytosolic GST A1/3, M1/3/5, P1, S1, T2, Z1 and microsomal GST 1/2/3
- CYP enzymes (CYP3A, CYP2C8, CYP1A2, and CYP2C9)

Excretion

Approximately 66% of radiolabeled ritlecitinib dose is excreted in the urine and 20% in the feces. Approximately 4% of the ritlecitinib dose is excreted unchanged drug in urine.

Specific Populations

No clinically relevant differences in the pharmacokinetics of ritlecitinib were observed based on age (12-73 years), body weight, gender, GST genotype, and race.

Patients with Renal Impairment

The AUC24 observed in patients with severe renal impairment (eGFR <30 mL/min) was 55.2% higher compared with the AUC24 in matched participants with normal renal functions. These differences are not considered clinically significant. Ritlecitinib has not been studied in patients with mild (eGFR 60 to <90 mL/min) or moderate (eGFR 30 to <60 mL/min) renal impairment, as a clinically relevant increase in ritlecitinib exposure is not expected in these patients. The eGFR and classification of renal function status of patients was done using the Modification of Diet in Renal Disease (MDRD) formula. Ritlecitinib has not been studied in patients with ESRD or in renal transplant recipients.

Patients with Hepatic Impairment

Patients with moderate (Child Pugh B) hepatic impairment had an 18.5% increase in ritlecitinib AUC24 compared to patients with normal hepatic function. Ritlecitinib has not been studied in patients with mild (Child Pugh A) hepatic impairment, as a clinically relevant increase in ritlecitinib exposure is not expected in these patients.

Ritlecitinib has not been studied in patients with severe (Child Pugh C) hepatic impairment and is not recommended for use in these patients [see Dosage and Administration (2.3) and Use In Specific Populations (8.6)].

Drug Interaction Studies

Clinical Studies

Effect of other drugs on ritlecitinib

The effect of coadministered drugs on the pharmacokinetics of ritlecitinib is presented in Table 5.

Table 5. Change in Pharmacokinetics of Ritlecitinib in the Presence of Coadministered Drugs
Coadministered Drugs | Regimen of Coadministered Drug | Dose of Ritlecitinib | Ratio [Ratios for Cmax and AUCinf compare coadministration of ritlecitinib with the drug versus administration of ritlecitinib alone.] (90% Confidence Interval)
Coadministered Drugs | Regimen of Coadministered Drug | Dose of Ritlecitinib | Cmax | AUCinf
Strong CYP3A inhibitor: Itraconazole [Drug interaction with CYP3A inhibitor is not clinically significant.] | 200 mg once daily × 5 days | 30 mg | 1.03 (0.83, 1.27) | 1.15 (1.05, 1.27)
Strong CYP enzyme inducer: Rifampin | 600 mg once daily × 8 days | 50 mg | 0.75 (0.63, 0.89) | 0.56 (0.52, 0.60)

Effect of ritlecitinib on other drugs

The effect of ritlecitinib on the pharmacokinetics of coadministered drugs is presented in Table 6.

Table 6. Change in Pharmacokinetics of Coadministered Drugs in the Presence of Ritlecitinib
Coadministered Drugs | Dose Regimen of Ritlecitinib | Ratio [Ratios for Cmax and AUCinf compare coadministration of the drug with ritlecitinib versus administration of the drug alone.] (90% Confidence Interval)
Coadministered Drugs | Dose Regimen of Ritlecitinib | Cmax | AUCinf
Oral contraceptive: Ethinyl estradiol (EE) and levonorgestrel (LN) [Drug interactions with ritlecitinib for oral contraceptives, CYP2B6 substrates, CYP2C substrates, and substrates of OATP1B1, BCRP, OAT3, and OCT1 transporters are not clinically significant.] | 50 mg once daily × 11 days | EE: 0.92 (0.84, 1.01); LN: 0.80 (0.73, 0.88) | EE: 0.98 (0.91, 1.06); LN [AUClast of levonorgestrel was reported in lieu of AUCinf because the terminal phase of levonorgestrel was not well characterized.] : 0.88 (0.83, 0.93)
Sensitive CYP3A substrate: Midazolam [see Drug Interactions (7.1)] | 200 mg once daily × 11 days [Ritlecitinib dosage 4 times the approved recommended dosage.] | 1.81 (1.48, 2.21) | 2.69 (2.16, 3.36)
Sensitive CYP1A2 substrate: Caffeine [see Drug Interactions (7.1)] | 200 mg once daily × 9 days | 1.10 (1.04, 1.16) | 2.65 (2.34, 3.00)
Sensitive CYP2B6 substrate: Efavirenz | 200 mg once daily × 11 days | 0.88 (0.77, 1.01) | 1.00 [AUC0-72 of efavirenz was reported] (0.95, 1.04)
Sensitive CYP2C substrate: Tolbutamide | 200 mg once daily × 10 days | 1.03 (0.97, 1.10) | 0.99 (0.92, 1.07)
Sensitive OATP1B1, BCRP and OAT3 substrate: Rosuvastatin | 200 mg once daily × 10 days | 0.73 (0.63, 0.83) | 0.87 (0.75, 1.01)
Sensitive OCT1 substrate: Sumatriptan | 400 mg single dose coadministration [Ritlecitinib dosage 8 times the approved recommended dosage.] | 0.87 (0.73, 1.03) | 1.30 (1.17, 1.44)
Sensitive OCT1 substrate: Sumatriptan | 400 mg single dose 8 hours prior to Sumatriptan | 1.50 (1.26, 1.78) | 1.50 (1.35, 1.66)

In Vitro Studies

CYP Related Pathways: Ritlecitinib is not an inhibitor of CYP2D6.

Other Metabolic Pathways: Ritlecitinib is not an inhibitor of uridine 5’ diphospho glucuronosyltransferases (UGTs) (UGT1A1, UGT1A4, UGT1A6, UGT1A9, and UGT2B7), GSTs or sulfotransferases (SULTs).

Transporter Systems: Ritlecitinib is not an inhibitor of P-glycoprotein (P-gp) or bile salt export pump (BSEP).

13 NONCLINICAL TOXICOLOGY

13.1 Carcinogenesis, Mutagenesis, Impairment of Fertility

In a 2-year rat carcinogenicity study, ritlecitinib increased the incidence of combined benign and malignant thymomas in female rats, and thyroid follicular adenomas and combined follicular adenomas and carcinomas in male rats at 100 mg/kg/day (29 times the MRHD based on AUC comparison). No ritlecitinib-related tumors were noted at doses up to 30 mg/kg/day (6.3 times the MRHD based on AUC comparison). No ritlecitinib-related tumors were noted in a 6-month Tg.rasH2 mouse carcinogenicity study at doses up to 300 mg/kg/day.

Ritlecitinib was not mutagenic in the in vitro bacterial reverse mutation assay (Ames assay). Ritlecitinib was positive in an in vitro micronucleus assay in TK6 cells. However, mechanistic studies determined that ritlecitinib is aneugenic and does not present a clinically relevant genotoxic concern. Additionally, in an in vivo rat bone marrow micronucleus assay, ritlecitinib was not aneugenic or clastogenic at doses up to 400 mg/kg/day.

Ritlecitinib had no effects on female rat fertility at doses up to 200 mg/kg/day (55 times the MRHD based on AUC comparison). Effects on male rat fertility were noted (higher preimplantation loss resulting in lower number of implantation sites and corresponding lower litter size in naïve females mated with ritlecitinib-dosed males) at 200 mg/kg/day (55 times the MRHD based on AUC comparison). No effects on male fertility were noted at doses up to 60 mg/kg/day (14 times the MRHD based on AUC comparison). No effects on spermatogenesis (sperm counts, production rate, motility, or morphology) were noted at any dose.

13.2 Animal Toxicology and Pharmacology

In two 9-month oral repeat dose toxicity studies in dogs, dose-related reversible axonal dystrophy was noted in the brainstem, spinal cord, sciatic nerve, nerve branches of the vagus nerve, and myenteric/submucosal plexuses of the GI tract at doses ≥20 mg/kg/day (14 times the MRHD based on AUC comparison). At 40 mg/kg/day (33 times the MRHD based on AUC comparison), ritlecitinib-related axonal dystrophy caused adverse reversible hearing loss and waveform deficits in brainstem auditory evoked potential (BAEP) testing. BAEP deficits were first noted during Month 7 of dosing and persisted through the end of dosing. No auditory threshold deficits were noted at 6 months after the end of dosing. No BAEP deficits were noted at doses ≤20 mg/kg/day. Additional mechanistic studies provided preliminary evidence that ritlecitinib-related hearing loss was not directly caused by JAK3 or TEC family kinase inhibition, but did not identify the underlying mechanism of axonal dystrophy in dogs.

14 CLINICAL STUDIES

The efficacy and safety of LITFULO were evaluated in one randomized, double-blind, placebo-controlled trial (Trial AA-I) in subjects 12 years of age and older with alopecia areata with ≥50% scalp hair loss, including alopecia totalis (AT) and alopecia universalis (AU).

Trial AA-I evaluated a total of 718 subjects who were randomized to one of the following treatment regimens for 48 weeks: 1) 200 mg once daily for 4 weeks followed by 50 mg once daily for 44 weeks; 2) 200 mg once daily for 4 weeks followed by 30 mg once daily for 44 weeks; 3) 50 mg once daily for 48 weeks; 4) 30 mg once daily for 48 weeks; 5) 10 mg once daily for 48 weeks; 6) placebo for 24 weeks followed by 200 mg once daily for 4 weeks and 50 mg once daily for 20 weeks; or 7) placebo for 24 weeks followed by 50 mg once daily for 24 weeks.

The recommended dose of LITFULO is 50 mg once daily and the results for this dose are discussed below.

Across all treatment groups 62% of subjects were female, 68% were White, 26% were Asian, and 4% were Black or African American. The majority of subjects (85%) were adults (≥18 years of age) with a mean age of 33.7 years. A total of 105 (15%) subjects 12 to <18 years of age and 20 (3%) subjects 65 years of age and older were enrolled. The mean baseline Severity of Alopecia Tool (SALT) score ranged from 88.3 to 93.0 across treatment groups; among subjects without AT/AU at baseline, the mean SALT score ranged from 78.3 to 87.0. The majority of subjects had abnormal eyebrows (83%) and eyelashes (75%) at baseline across treatment groups. The median duration since alopecia areata diagnosis was 6.9 years and the median duration of the current alopecia areata episode was 2.5 years. Randomization was stratified by AT/AU status with 46% of subjects classified as AT/AU based upon a baseline SALT score of 100.

Clinical Response

Assessment of scalp hair loss was based on the SALT score. At Week 24, a greater proportion of subjects had a SALT ≤20 response (20% or less of scalp hair loss) and SALT ≤10 response (10% or less of scalp hair loss) with LITFULO compared to placebo (Table 7). The percentage of subjects achieving SALT ≤20 response by visit is shown in Figure 1.

Table 7. Proportion of Subjects with Response on the SALT Scale at Week 24
 | LITFULO 50 mg QD (N=130) % Responders | Placebo (N=131) % Responders | Difference from Placebo (95% CI)
SALT ≤20 response [SALT ≤20 responders were subjects with scalp hair loss of ≤20%. SALT scores range from 0 to 100 with 0 = no scalp hair loss and 100 = total scalp hair loss.] | 23.0 | 1.6 | 21.4 (13.4, 29.5)
SALT ≤10 response [SALT ≤10 responders were subjects with scalp hair loss of ≤10%.] | 13.4 | 1.5 | 11.9 (5.4, 18.3)
Abbreviations: CI = confidence interval; N = total number of subjects; QD = once daily; SALT = Severity of Alopecia Tool.

Figure 1. SALT ≤20 Response through Week 24

Abbreviations: QD = once daily; SALT = Severity of Alopecia Tool.

16 HOW SUPPLIED/STORAGE AND HANDLING

LITFULO capsules are packaged in child-resistant, white, high-density polyethylene (HDPE) bottles with polypropylene (PP) cap with a foil heat induction seal liner. The bottles contain 1g of desiccant in a high-density polyethylene (HDPE) canister. Do not eat the desiccant.

Dosage Form | Strength | Description | Bottle Size; (number of capsules) | NDC Number
Capsules | 50 mg of ritlecitinib | Size 3, opaque capsules with yellow body and blue cap. The body is printed with “RCB 50” and the cap is printed with “Pfizer” in black. | 28 count bottle | 0069-0334-28

STORAGE AND HANDLING

Store LITFULO at 20°C to 25°C (68°F to 77°F), excursions permitted between 15°C to 30°C (59°F to 86°F) [See USP Controlled Room Temperature]. Keep in original package.

17 PATIENT COUNSELING INFORMATION

Advise the patient to read the FDA-approved patient labeling (Medication Guide).

Administration

Advise patients not to crush, split or chew LITFULO capsules [see Dosage and Administration (2.2)].

Serious Infections

Inform patients that they may develop infections when taking LITFULO which in some cases can be serious. Instruct patients to tell their healthcare provider if they develop any signs or symptoms of an infection [see Warnings and Precautions (5.1)].

Advise patients that the risk of herpes zoster is increased in patients treated with LITFULO [see Warnings and Precautions (5.1)].

Malignancies

Inform patients that LITFULO may increase their risk of certain cancers, including skin cancers. Periodic skin examinations are recommended while using LITFULO [see Warnings and Precautions (5.3)].

Thromboembolic Events

Advise patients that events of PE and retinal artery occlusion have been reported in clinical trials with LITFULO. Instruct patients to seek immediate medical attention if they develop any signs or symptoms of a thrombosis [see Warnings and Precautions (5.5)].

Hypersensitivity Reactions

Advise patients to discontinue LITFULO and seek immediate medical attention if they develop any signs and symptoms of serious allergic reaction [see Warnings and Precautions (5.6)].

Laboratory Abnormalities

Inform patients that LITFULO may affect certain lab tests, and that blood tests are required before and during LITFULO treatment [see Dosage and Administration (2.1) and Warnings and Precautions (5.7)].

Vaccinations

Advise patients that vaccination with live vaccines is not recommended during LITFULO treatment and shortly prior to LITFULO treatment. Instruct patients to inform the healthcare practitioner that they are taking LITFULO prior to a potential vaccination [see Warnings and Precautions (5.8)].

Pregnancy

Advise pregnant females and females of reproductive potential to inform their healthcare providers if they are pregnant or intend to becomes pregnant during treatment with LITFULO. Instruct patients to report their pregnancy to Pfizer Inc. at 1-877-390-2940 [see Use in Specific Populations (8.1)].

Lactation

Advise women not to breastfeed during treatment with LITFULO and for 14 hours after the last dose [see Use in Specific Populations (8.2)].

For Medical Information about LITFULO, please visit www.pfizermedinfo.com or call 1-800-438-1985.

LAB-1469-1.0

Medication Guide
LITFULO™ (lit-FUL-oh)
(ritlecitinib)
capsules, for oral use

What is the most important information I should know about LITFULO?

LITFULO may cause serious side effects, including:

1. Serious infections

LITFULO is a medicine that affects your immune system. LITFULO can lower the ability of your immune system to fight infections. Some people have had serious infections while taking LITFULO or other similar medicines, including tuberculosis (TB), and infections caused by bacteria, fungi, or viruses that can spread throughout the body and have been hospitalized. Some people taking similar medicines to LITFULO have died from these infections.

- Your healthcare provider should test you for TB before starting treatment with LITFULO.
- Your healthcare provider should watch you closely for signs and symptoms of TB during treatment with LITFULO.

You should not start taking LITFULO if you have any kind of infection unless your healthcare provider tells you it is okay.

You may be at a higher risk of developing shingles (herpes zoster).

Before starting LITFULO, tell your healthcare provider if you:

- are being treated for an infection.
- have an infection that has not gone away or that keeps coming back.
- have diabetes, chronic lung disease, HIV, or a weak immune system.
- have TB or have been in close contact with someone with TB.
- have had shingles (herpes zoster).
- have had hepatitis B or hepatitis C.
- live or have lived or have traveled to certain parts of the country (such as the Ohio and Mississippi River valleys and the Southwest) where there is an increased chance for getting certain kinds of fungal infections. These infections may happen or become more severe if you use LITFULO. Ask your healthcare provider if you do not know if you have lived in an area where these infections are common.
- think you have an infection or have symptoms of an infection such as:

- fever, sweating, or chills
- muscle aches
- cough or shortness of breath

- blood in your phlegm
- weight loss
- warm, red, or painful skin or sores on your body

- diarrhea or stomach pain
- burning when you urinate or urinating more often than usual
- feeling very tired

After starting LITFULO, call your healthcare provider right away if you have any symptoms of an infection. LITFULO can make you more likely to get infections or make any infections that you have worse. If you get a serious infection, your healthcare provider may stop treatment with LITFULO until your infection is controlled.

2. Increased risk of death in people 50 years of age and older who have at least 1 heart disease (cardiovascular) risk factor and are taking a medicine in the class of medicines called Janus kinase (JAK) inhibitors. LITFULO is a kinase inhibitor medicine.

3. Cancer and immune system problems

LITFULO may increase your risk of certain cancers by changing the way your immune system works.

- Lymphoma and other cancers, including skin cancers, can happen in people taking LITFULO.
- People taking a medicine in the class of medicines called JAK inhibitors have a higher risk of certain cancers including lymphoma and lung cancer, especially if you are current or past smoker.
- Follow your healthcare provider’s advice about having your skin checked for skin cancer during treatment with LITFULO.

Tell your healthcare provider if you have ever had any type of cancer.

4. Increased risk of major cardiovascular events such as heart attack, stroke, or death in people 50 years of age and older who have at least 1 heart disease (cardiovascular) risk factor and taking a medicine in the class of medicines called JAK inhibitors, especially if you are a current or past smoker.

Get emergency help right away if you have any symptoms of a heart attack or stroke while using LITFULO, including:

- discomfort in the center of your chest that lasts for more than a few minutes, or that goes away and comes back
- severe tightness, pain, pressure, or heaviness in your chest, throat, neck, or jaw
- pain or discomfort in your arms, back, neck, jaw, or stomach
- shortness of breath with or without chest discomfort
- breaking out in a cold sweat
- nausea or vomiting
- feeling lightheaded
- weakness in one part or on one side of your body
- slurred speech

5. Blood clots

Blood clots in the veins of your legs (deep vein thrombosis, DVT), lungs (pulmonary embolism, PE), or eyes can happen in some people taking LITFULO. This may be life-threatening. Blood clots in the veins of the legs (deep vein thrombosis, DVT) and lungs (pulmonary embolism, PE) have happened more often in people who are 50 years of age and older with at least 1 heart disease (cardiovascular) risk factor taking a medicine in the class of medicines called JAK inhibitors.

- Tell your healthcare provider if you have had blood clots in the past.
- Stop taking LITFULO and get medical help right away if you have any signs and symptoms of blood clots during treatment with LITFULO, including:
  - swelling, pain or tenderness in one or both legs
  - sudden, unexplained chest or upper back pain
  - shortness of breath or difficulty breathing
  - changes in vision, especially in one eye only

6. Allergic reactions

Symptoms that may mean you are having an allergic reaction have been seen during treatment with LITFULO. Some of these reactions were serious. Stop taking LITFULO and get emergency medical help right away if you have symptoms of allergic reaction, including:

- hives
- rash
- trouble breathing

- feeling faint or dizzy
- swelling of your lips, tongue, or throat

7. Changes in certain laboratory test results

Your healthcare provider should do blood tests before you start taking LITFULO and during treatment to check for the following:

- low lymphocyte count. Lymphocytes are white blood cells that help the body fight off infections.
- low platelet count. Platelets help form clots and stop or prevent bleeding.
- elevated liver enzymes. Liver enzymes help to tell if your liver is functioning normally. Elevated liver enzymes may indicate that your healthcare provider needs to do additional tests on your liver.
- increased creatine phosphokinase (CPK). Increased CPK levels in the blood are common with LITFULO and can also be severe.

You should not take LITFULO if your lymphocyte counts or platelet counts are too low or your liver tests are too high. Your healthcare provider may stop your LITFULO treatment for a period of time if needed because of changes in these blood test results.

See "What are the possible side effects of LITFULO?" for more information about side effects.

What is LITFULO?

LITFULO is a prescription medicine that is a kinase inhibitor. LITFULO is used to treat an immune system problem that causes severe hair loss (alopecia areata) in adults and children 12 years and older.

It is not known if LITFULO is safe and effective in children under 12 years of age.

Before taking LITFULO, tell your healthcare provider about all of your medical conditions, including if you:

- See "What is the most important information I should know about LITFULO?"
- have an infection
- are a current or past smoker
- have had a heart attack, other heart problems, or stroke
- have liver problems
- have low platelet counts or white blood cell counts
- have recently received or are scheduled to receive an immunization (vaccine). People who take LITFULO should not receive live vaccines during treatment or right before starting treatment with LITFULO.
- are pregnant or plan to become pregnant. It is not known if LITFULO will harm your unborn baby.
  Females who are able to become pregnant:
  - Tell your healthcare provider if you are pregnant or plan to become pregnant during treatment with LITFULO.
  - There is a pregnancy registry for people who take LITFULO during pregnancy. Report pregnancies to Pfizer Inc. at 1-877-390-2940.
- are breastfeeding or plan to breastfeed. It is not known if LITFULO passes into your breast milk. Do not breastfeed during treatment with LITFULO and for 14 hours after your last dose of LITFULO. Talk to your healthcare provider about the best way to feed your baby during treatment with LITFULO.

Tell your healthcare provider about all the medicines you take, including prescription and over-the-counter medicines, vitamins, and herbal supplements. LITFULO and other medicines may affect each other causing side effects.

Know the medicines you take. Keep a list of them to show your healthcare provider and pharmacist whenever

you get a new medicine.

How should I take LITFULO?

- Take LITFULO exactly as your healthcare provider tells you to take it.
- Take LITFULO 1 time each day, with or without food.
- Swallow LITFULO capsules whole. Do not crush, split, or chew the capsules.
- If you miss a dose of LITFULO, take the missed dose as soon as you remember. If it is less than 8 hours before your next scheduled dose of LITFULO, skip the missed dose and take the next dose at your usual time.

If you take too much LITFULO, call the Poison Control Center at 1-800-222-1222 or go to the nearest hospital emergency room right away.

What are the possible side effects of LITFULO?

LITFULO may cause serious side effects, including:

See "What is the most important information I should know about LITFULO?"

The most common side effects of LITFULO include:

- headache
- diarrhea
- acne
- rash

- hives
- inflamed hair pores (folliculitis)
- fever
- eczema

- dizziness
- shingles
- decreased red blood cell counts
- mouth sores, redness and swelling of the lining of your mouth

These are not all the possible side effects of LITFULO.

Call your doctor for medical advice about side effects. You may report side effects to FDA at 1-800-FDA-1088.

You may also report side effects to Pfizer at 1-800-438-1985.

How should I store LITFULO?

- Store LITFULO at room temperature between 68°F to 77°F (20°C to 25°C).
- Keep LITFULO in the original package.
- The LITFULO bottle has a child resistant closure and contains a cannister with a drying agent (desiccant). Do not eat the desiccant.

Keep LITFULO and all medicines out of the reach of children.

General information about the safe and effective use of LITFULO.

Medicines are sometimes prescribed for purposes other than those listed in a Medication Guide. Do not use LITFULO for a condition for which it was not prescribed. Do not give LITFULO to other people, even if they have the same symptoms you have. It may harm them. You can ask your pharmacist or healthcare provider for information about LITFULO that is written for health professionals.

What are the ingredients in LITFULO?
Active ingredient: ritlecitinib
Inactive ingredients: crospovidone, glyceryl dibehenate, lactose monohydrate, microcrystalline cellulose, and hypromellose (HPMC) capsule shells. The yellow/blue, opaque capsule shells contain Brilliant blue FCF – FD&C Blue, hypromellose, titanium dioxide, and yellow iron oxide.

LAB-1525-1.0

This Medication Guide has been approved by the U.S. Food and Drug Administration.

Issued: 6/2023

PRINCIPAL DISPLAY PANEL - 50 mg Capsule Bottle Label

ALWAYS DISPENSE WITH MEDICATION GUIDE

Pfizer
NDC 0069-0334-28

Litfulo™
(ritlecitinib) capsules

50 mg*

Do not crush, split, or chew
the capsules.
Do not eat the desiccant.

28 Capsules Rx only